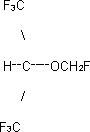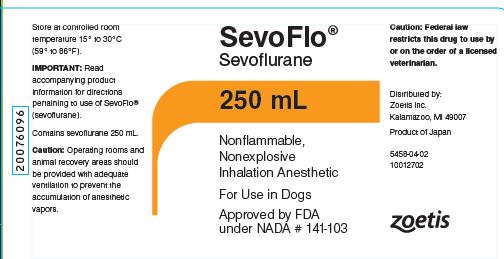 DRUG LABEL: SevoFlo
NDC: 54771-5458 | Form: INHALANT
Manufacturer: Zoetis Inc.
Category: animal | Type: PRESCRIPTION ANIMAL DRUG LABEL
Date: 20230717

ACTIVE INGREDIENTS: SEVOFLURANE 1 mL/1 mL

SevoFlo®

SevoFlo®

(sevoflurane)

Inhalation Anesthetic For Use in Dogs

Caution: Federal law restricts this drug to use by or on the order of a licensed veterinarian.

DESCRIPTION:

SevoFlo (sevoflurane) is a volatile liquid, is a halogenated general inhalation anesthetic drug. Its chemical name is fluoromethyl 2,2,2-trifluoro-l-(trifluoromethyl) ethyl ether, and its structural formula is:

Sevoflurane Physical Constants are:

Molecular Weight |  | 200.05
Boiling Point at 760 mm Hg |  | 58.6°C
Specific Gravity at 20 °C |  | 1.520 - 1.525 g/mL
Vapor Pressure in mm Hg | at 20 °C | 157
 | at 25°C | 197
 | at 36°C | 317
Distribution Partition Coefficients | at 37°C:
Blood/Gas |  | 0.63 - 0.69
Water/Gas |  | 0.36
Olive Oil/Gas |  | 47 - 54
Brain/Gas |  | 1.15
Mean Component/Gas Partition Coefficients at 25°C for Polymers Used Commonly in Medical Applications:
Conductive rubber |  | 14.0
Butyl rubber |  | 7.7
Polyvinyl chloride |  | 17.4
Polyethylene |  | 1.3

Sevoflurane is nonflammable and nonexplosive as defined by the requirements of International Electrotechnical Commission 601-2-13.
Sevoflurane is a clear, colorless, stable liquid containing no additives or chemical stabilizers. Sevoflurane is nonpungent. It is miscible with ethanol, ether, chloroform and petroleum benzene, and it is slightly soluble in water. Sevoflurane is stable when stored under normal room lighting condition according to instructions.

INDICATIONS:

SevoFlo is indicated for induction and maintenance of general anesthesia in dogs.

DOSAGE AND ADMINISTRATION:

Inspired Concentration: The delivered concentration of SevoFlo should be known. Since the depth of anesthesia may be altered easily and rapidly, only vaporizers producing predictable percentage concentrations of sevoflurane should be used. Sevoflurane should be vaporized using a precision vaporizer specifically calibrated for sevoflurane. Sevoflurane contains no stabilizer. Nothing in the drug product alters calibration or operation of these vaporizers. The administration of general anesthesia must be individualized based on the patient's response. WHEN USING SEVOFLURANE, PATIENTS SHOULD BE CONTINUOUSLY MONITORED AND FACILITIES FOR MAINTENANCE OF PATENT AIRWAY, ARTIFICIAL VENTILATION, AND OXYGEN SUPPLEMENTATION MUST BE IMMEDIATELY AVAILABLE.

Replacement of Desiccated CO2 Absorbents: When a clinician suspects that the CO2 absorbent may be desiccated, it should be replaced. An exothermic reaction occurs when sevoflurane is exposed to CO2 absorbents. This reaction is increased when the CO2 absorbent becomes desiccated (see PRECAUTIONS).

Premedication: No specific premedication is either indicated or contraindicated with sevoflurane. The necessity for and choice of premedication is left to the discretion of the veterinarian. Preanesthetic doses for premedicants may be lower than the label directions for their use as a single medication.^1

Induction: For mask induction using sevoflurane alone, inspired concentrations of up to 7% sevoflurane with oxygen are employed to induce surgical anesthesia in the healthy dog. These concentrations can be expected to produce surgical anesthesia in 3 to 14 minutes. Due to the rapid and dose dependent changes in anesthetic depth, care should be taken to prevent overdosing. Respiration must be monitored closely in the dog and supported when necessary with supplemental oxygen and/or assisted ventilation.

Maintenance: SevoFlo may be used for maintenance anesthesia following mask induction using sevoflurane or following injectable induction agents. The concentration of vapor necessary to maintain anesthesia is much less than that required to induce it.

Surgical levels of anesthesia in the healthy dog may be maintained with inhaled concentrations of 3.7-4.0% sevoflurane in oxygen in the absence of premedication and 3.3-3.6% in the presence of premedication. The use of injectable induction agents without premedication has little effect on the concentrations of sevoflurane required for maintenance. Anesthetic regimens that include opioid, alpha2- agonist, benzodiazepine or phenothiazine premedication will allow the use of lower sevoflurane maintenance concentrations.

CONTRAINDICATIONS:

SevoFlo is contraindicated in dogs with a known sensitivity to sevoflurane or other halogenated agents.

WARNINGS:

Sevoflurane is a profound respiratory depressant.
DUE TO THE RAPID AND DOSE DEPENDENT CHANGES IN ANESTHETIC DEPTH, RESPIRATION MUST BE MONITORED CLOSELY IN THE DOG AND SUPPORTED WHEN NECESSARY WITH SUPPLEMENTAL OXYGEN AND/OR ASSISTED VENTILATION.

In cases of severe cardiopulmonary depression, discontinue drug administration, ensure the existence of a patent airway and initiate assisted or controlled ventilation with pure oxygen. Cardiovascular depression should be treated with plasma expanders, pressor agents, antiarrhythmic agents or other techniques as appropriate for the observed abnormality.

Due to sevoflurane's low solubility in blood, increasing the concentration may result in rapid changes in anesthetic depth and hemodynamic changes (dose dependent decreases in respiratory rate and blood pressure) compared to other volatile anesthetics. Excessive decreases in blood pressure or respiratory depression may be corrected by decreasing or discontinuing the inspired concentration of sevoflurane.

Potassium hydroxide containing CO2 absorbents (e.g. BARALYME®) are not recommended for use with sevoflurane.

ADVERSE REACTIONS:

The most frequently reported adverse reactions during maintenance anesthesia were hypotension, followed by tachypnea, muscle tenseness, excitation, apnea, muscle fasciculations and emesis.

Infrequent adverse reactions include paddling, retching, salivation, cyanosis, premature ventricular contractions and excessive cardiopulmonary depression.

Transient elevations in liver function tests and white blood cell count may occur with sevoflurane, as with the use of other halogenated anesthetic agents.

PRECAUTIONS:

Halogenated volatile anesthetics can react with desiccated carbon dioxide (CO2) absorbents to produce carbon monoxide (CO) that may result in elevated carboxyhemoglobin levels in some patients. To prevent this reaction, sevoflurane should not be passed through desiccated soda lime or barium hydroxide lime.

Replacement of Desiccated CO2 Absorbents:
When a clinician suspects that the CO2 absorbent may be desiccated, it should be replaced before administration of sevoflurane. The exothermic reaction that occurs with sevoflurane and CO2 absorbents is increased when the CO2 absorbent becomes desiccated, such as after an extended period of dry gas flow through the CO2 absorbent canisters. Extremely rare cases of spontaneous fire in the respiratory circuit of the anesthesia machine have been reported during sevoflurane use in conjunction with the use of a desiccated CO2 absorbent, specifically those containing potassium hydroxide (e.g. BARALYME). Potassium hydroxide-containing CO2 absorbents are not recommended for use with sevoflurane. An unusually delayed rise in the inspired gas concentration (decreased delivery) of sevoflurane compared with the vaporizer setting may indicate excessive heating of the CO2 absorbent canister and chemical breakdown of sevoflurane. The color indicator of most CO2 absorbent may not change upon desiccation. Therefore, the lack of significant color change should not be taken as an assurance of adequate hydration. CO2 absorbents should be replaced routinely regardless of the state of the color indicator.

The use of some anesthetic regimens that include sevoflurane may result in bradycardia that is reversible with anticholinergics. Studies using sevoflurane anesthetic regimens that included atropine or glycopyrrolate as premedicants showed these anticholinergics to be compatible with sevoflurane in dogs.

During the induction and maintenance of anesthesia, increasing the concentration of sevoflurane produces dose dependent decreases in blood pressure and respiratory rate. Due to sevoflurane's low solubility in blood, these changes may occur more rapidly than with other volatile anesthetics. Excessive decreases in blood pressure or respiratory depression may be related to depth of anesthesia and may be corrected by decreasing the inspired concentration of sevoflurane. RESPIRATION MUST BE MONITORED CLOSELY IN THE DOG AND SUPPORTED WHEN NECESSARY WITH SUPPLEMENTAL OXYGEN AND/OR ASSISTED VENTILATION. The low solubility of sevoflurane also facilitates rapid elimination by the lungs.

The use of sevoflurane in humans increases both the intensity and duration of neuromuscular blockade induced by nondepolarizing muscle relaxants. The use of sevoflurane with nondepolarizing muscle relaxants has not been evaluated in dogs.

Compromised or debilitated dogs: Doses may need adjustment for geriatric or debilitated dogs. Because clinical experience in administering sevoflurane to dogs with renal, hepatic and cardiovascular insufficiency is limited, its safety in these dogs has not been established.

Breeding dogs: The safety of sevoflurane in dogs used for breeding purposes, during pregnancy, or in lactating bitches, has not been evaluated.

Neonates: The safety of sevoflurane in young dogs (less than 12 weeks of age) has not been evaluated.

HUMAN SAFETY:

Not for human use. Keep out of reach of children.

Operating rooms and animal recovery areas should be provided with adequate ventilation to prevent the accumulation of anesthetic vapors.

There is no specific work exposure limit established for sevoflurane. However, the National Institute for Occupational Safety and Health has recommended an 8 hour time-weighted average limit of 2 ppm for halogenated anesthetic agents in general.

Direct exposure to eyes may result in mild irritation. If eye exposure occurs, flush with plenty of water for 15 minutes. Seek medical attention if irritation persists.

Symptoms of human overexposure (inhalation) to sevoflurane vapors include respiratory depression, hypotension, bradycardia, shivering, nausea and headache. If these symptoms occur, remove the individual from the source of exposure and seek medical attention.

To report suspected adverse events, for technical assistance or to obtain a copy of the SDS, contact Zoetis Inc. at 1-888-963-8471 or www.zoetis.com.

For additional information about adverse drug experience reporting for animal drugs, contact FDA at 1-888-FDA-VETS or online at

http://www.fda.gov/AnimalVeterinary/SafetyHealth.

CLINICAL PHARMACOLOGY:

Sevoflurane is an inhalational anesthetic agent for induction and maintenance of general anesthesia. The Minimum Alveolar Concentration (MAC) of sevoflurane as determined in 18 dogs is 2.36%.^2 MAC is defined as that alveolar concentration at which 50% of healthy patients fail to respond to noxious stimuli. Multiples of MAC are used as a guide for surgical levels of anesthesia, which are typically 1.3 to 1.5 times the MAC value.

Because of the low solubility of sevoflurane in blood (blood/gas partition coefficient at 37°C = 0.63-0.69), a minimal amount of sevoflurane is required to be dissolved in the blood before the alveolar partial pressure is in equilibrium with the arterial partial pressure. During sevoflurane induction, there is a rapid increase in alveolar concentration toward the inspired concentration.

Sevoflurane produces only modest increases in cerebral blood flow and metabolic rate, and has little or no ability to potentiate seizures.^3 Sevoflurane has a variable effect on heart rate, producing increases or decreases depending on experimental conditions.^4,5 Sevoflurane produces dose-dependent decreases in mean arterial pressure, cardiac output and myocardial contraction.^6 Among inhalation anesthetics, sevoflurane has low arrhythmogenic potential.^7

Sevoflurane is chemically stable. No discernible degradation occurs in the presence of strong acids or heat. Sevoflurane reacts through direct contact with CO2 absorbents (soda lime and barium hydroxide lime) producing pentafluoroisopropenyl fluoromethyl ether (PIFE, C4H2F6O), also known as Compound A, and trace amounts of pentafluoromethoxy isopropyl fluoromethyl ether (PMFE, C5H6F6O), also known as Compound B.

Compound A:

The production of degradants in the anesthesia circuit results from the extraction of the acidic proton in the presence of a strong base (potassium hydroxide and/or NaOH) forming an alkene (Compound A) from sevoflurane.

Compound A is produced when sevoflurane interacts with soda lime or barium hydroxide lime. Reaction with barium hydroxide lime results in a greater production of Compound A than does reaction with soda lime. Its concentration in a circle absorber system increases with increasing sevoflurane concentrations and with decreasing fresh gas flow rates. Sevoflurane degradation in soda lime has been shown to increase with temperature. Since the reaction of carbon dioxide with absorbents is exothermic, this temperature increase will be determined by the quantities of CO2 absorbed, which in turn will depend on fresh gas flow in the anesthetic circle system, metabolic status of the patient and ventilation. Although Compound A is a dose-dependent nephrotoxin in rats, the mechanism of this renal toxicity is unknown. Two spontaneously breathing dogs under sevoflurane anesthesia showed increases in concentrations of Compound A as the oxygen flow rate was decreased at hourly intervals, from 500 mL/min (36 and 18 ppm Compound A) to 250 mL/min (43 and 31 ppm) to 50 mL/min (61 and 48 ppm).^8

Fluoride ion metabolite:

Sevoflurane is metabolized to hexafluoroisopropanol (HFIP) with release of inorganic fluoride and CO2. Fluoride ion concentrations are influenced by the duration of anesthesia and the concentration of sevoflurane. Once formed, HFIP is rapidly conjugated with glucuronic acid and eliminated as a urinary metabolite. No other metabolic pathways for sevoflurane have been identified. In humans, the fluoride ion half-life was prolonged in patients with renal impairment, but human clinical trials contained no reports of toxicity associated with elevated fluoride ion levels. In a study in which 4 dogs were exposed to 4% sevoflurane for 3 hours, maximum serum fluoride concentrations of 17.0-27.0 mcmole/L were observed after 3 hours of anesthesia. Serum fluoride fell quickly after anesthesia ended, and had returned to baseline by 24 hours post-anesthesia.
In a safety study, eight healthy dogs were exposed to sevoflurane for 3 hours/day, 5 days/week for 2 weeks (total 30 hours exposure) at a flow rate of 500 mL/min in a semiclosed, rebreathing system with soda lime. Renal toxicity was not observed in the study evaluation of clinical signs, hematology, serum chemistry, urinalysis, or gross or microscopic pathology.

DRUG INTERACTIONS:

In the clinical trial, sevoflurane was used safely in dogs that received frequently used veterinary products including steroids and heartworm and flea preventative products.

Intravenous Anesthetics: Sevoflurane administration is compatible with barbiturates, propofol and other commonly used intravenous anesthetics.

Benzodiazepines and Opioids: Benzodiazepines and opioids would be expected to decrease the MAC of sevoflurane in the same manner as other inhalational anesthetics. Sevoflurane is compatible with benzodiazepines and opioids as commonly used in surgical practice.

Phenothiazines and Alpha2- Agonists: Sevoflurane is compatible with phenothiazines and alpha2- agonists as commonly used in surgical practice.

In a laboratory study, the use of the acepromazine/oxymorphone/thiopental/sevoflurane anesthetic regimen resulted in prolonged recoveries in eight (of 8) dogs compared to recoveries from sevoflurane alone.

CLINICAL EFFECTIVENESS:

The effectiveness of sevoflurane was investigated in a clinical study involving 196 dogs. Thirty dogs were mask-induced with sevoflurane using anesthetic regimens that included various premedicants. During the clinical study, one hundred sixty-six dogs received sevoflurane maintenance anesthesia as part of several anesthetic regimens that used injectable induction agents and various premedicants.

The duration of anesthesia and the choice of anesthetic regimens were dependent upon the procedures that were performed. Duration of anesthesia ranged from 16 to 424 minutes among the individual dogs. Sevoflurane vaporizer concentrations during the first 30 minutes of maintenance anesthesia were similar among the various anesthetic regimens. The quality of maintenance anesthesia was considered good or excellent in 169 out of 196 dogs.

The table shows the average vaporizer concentrations and oxygen flow rates during the first 30 minutes for all sevoflurane maintenance anesthesia regimens:

Average Vaporizer Concentrations among Anesthetic Regimens | Average Vaporizer Concentrations among Individual Dogs | Average Oxygen Flow Rates among Anesthetic Regimens | Average Oxygen Flow Rates among Individual Dogs
3.31 - 3.63% | 1.6 - 5.1% | 0.97 - 1.31 L/minute | 0.5 - 3.0 L/minute

During the clinical trial, when a barbiturate was used for induction, the times to extubation, sternal recumbency and standing recovery were longer for dogs that received anesthetic regimens containing two preanesthetics compared to regimens containing one preanesthetic. Recovery times were shorter when anesthetic regimens used sevoflurane or propofol for induction. The quality of recovery was considered good or excellent in 184 out of 196 dogs.

Anesthetic regimen drug dosages, physiological responses, and the quality of induction, maintenance and recovery were comparable between 10 sighthounds and other breeds evaluated in the study. During the clinical study there was no indication of prolonged recovery times in the sighthounds.

HOW SUPPLIED:

SevoFlo (sevoflurane) is packaged in amber colored bottles containing 100 ml and 250 mL sevoflurane, List 5458.

STORAGE CONDITIONS:

Store at controlled room temperature 15°-30°C (59°-86°F).

REFERENCES:

1. Plumb, D.C. ed., Veterinary Drug Handbook, Second Edition, University of Iowa Press, Ames, IA: p. 424 (1995).

2. Kazama, T. and Ikeda, K., Comparison of MAC and the rate of rise of alveolar concentration of sevoflurane with halothane and isoflurane in the dog. Anesthesiology. 68: 435-437 (1988).

3. Scheller, M.S., Nakakimura, K., Fleischer, J.E. and Zornow, M.H., Cerebral effects of sevoflurane in the dog: Comparison with isoflurane and enflurane. Brit. J. Anesthesia 65: 388-392 (1990).

4. Frink, E.J., Morgan, S.E., Coetzee, A., Conzen, P.F. and Brown, B.R., Effects of sevoflurane, halothane, enflurane and isoflurane on hepatic blood flow and oxygenation in chronically instrumented greyhound dogs. Anesthesiology 76: 85-90 (1992).

5. Kazama, T. and Ikeda, K., The comparative cardiovascular effects of sevoflurane with halothane and isoflurane. J. Anesthesiology 2: 63-8 (1988).

6. Bernard, J. M., Wouters, P.F., Doursout, M.F., Florence, B., Chelly, J.E. and Merin, R.G., Effects of sevoflurane on cardiac and coronary dynamics in chronically instrumented dogs. Anesthesiology 72: 659-662 (1990).

7. Hayaski, Y., Sumikawa, K., Tashiro, C., Yamatodani, A. and Yoshiya, I., Arrhythmogenic threshold of epinephrine during sevoflurane, enflurane and isoflurane anesthesia in dogs. Anesthesiology 69: 145-147 (1988).

8. Muir, W.W. and Gadawski, J., Cardiorespiratory effects of low-flow and closed circuit inhalation anesthesia, using sevoflurane delivered with an in-circuit vaporizer and concentrations of compound A. Amer. J. Vet. Res. 59 (5): 603-608 (1998).

Approved by FDA under NADA # 141-103
Distributed by:
Zoetis Inc.
Kalamazoo, MI 49007
Product of Japan
To report suspected adverse events, for technical assistance or to obtain a copy of the SDS, contact Zoetis Inc. at 1-888-963-8471 or www.zoetis.com.
For additional information about adverse drug experience reporting for animal drugs, contact FDA at 1-888-FDA-VETS or online at www.fda.gov/reportanimalae.
Revised: June 2019
50934000

PRINCIPAL DISPLAY PANEL - CARTON

10012702